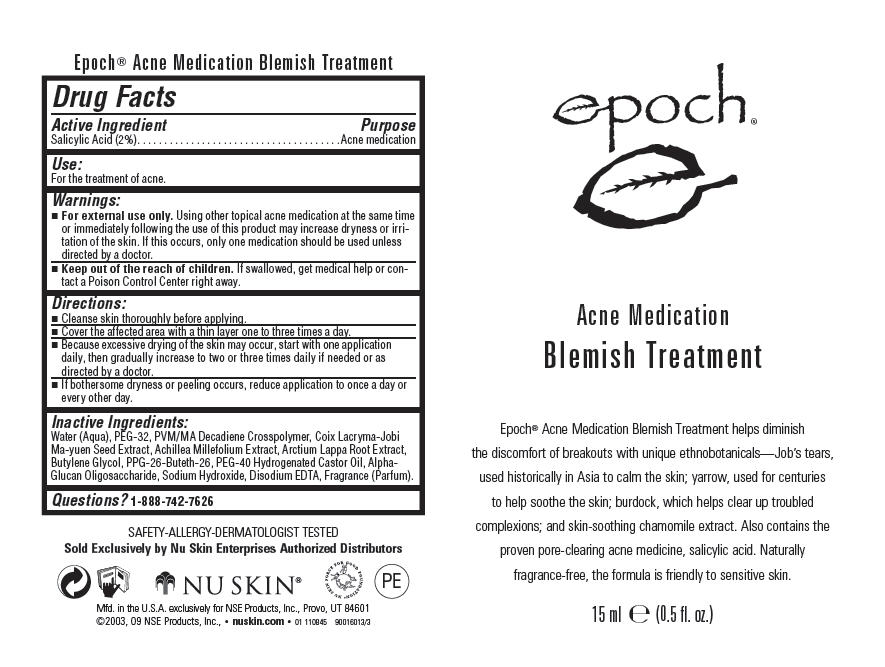 DRUG LABEL: Epoch
NDC: 62839-1084 | Form: GEL
Manufacturer: NSE Products, Inc.
Category: otc | Type: HUMAN OTC DRUG LABEL
Date: 20110324

ACTIVE INGREDIENTS: Salicylic Acid 20 g/1000 mL
INACTIVE INGREDIENTS: Water; POLYETHYLENE GLYCOL 1500; Coix Lacryma-Jobi Var. Ma-Yuen Seed; Achillea Millefolium; Arctium Lappa Root; Butylene Glycol; Polyoxyl 40 Hydrogenated Castor Oil; Sodium Hydroxide; Edetate Disodium

Epoch® Acne Medication Blemish Treatment

Drug Facts

Active Ingredient

Salicylic Acid (2%)

Purpose

Acne medication

Use

For the treatment of acne.

Warnings

WHEN USING

- For external use only. Using other topical acne medication at the same time or immediately following the use of this product may increase dryness or irritation of the skin. If this occurs, only one medication should be used unless directed by a doctor.

KEEP OUT OF REACH OF CHILDREN

- Keep out of the reach of children. If swallowed, get medical help or contact a Poison Control Center right away.

Directions

- Cleanse skin thoroughly before applying.
- Cover the affected area with a thin layer one to three times a day.
- Because excessive drying of the skin may occur, start with one application daily, then gradually increase to two or three times daily if needed or as directed by a doctor.
- If bothersome dryness or peeling occurs, reduce application to once a day or every other day.

Inactive Ingredients

Water (Aqua), PEG-32, PVM/MA Decadiene Crosspolymer, Coix Lacryma-Jobi Ma-yuen Seed Extract, Achillea Millefolium Extract, Arctium Lappa Root Extract, Butylene Glycol, PPG-26-Buteth-26, PEG-40 Hydrogenated Castor Oil, Alpha-Glucan Oligosaccharide, Sodium Hydroxide, Disodium EDTA, Fragrance (Parfum).

Questions?

1-888-742-7626

PRINCIPAL DISPLAY PANEL - 15 ml Tube Label

epoch ®

Acne Medication

Blemish Treatment

Epoch® Acne Medication Blemish Treatment helps diminish
the discomfort of breakouts with unique ethnobotanicals—Job's tears,
used historically in Asia to calm the skin; yarrow, used for centuries
to help soothe the skin; burdock, which helps clear up troubled
complexions; and skin-soothing chamomile extract. Also contains the
proven pore-clearing acne medicine, salicylic acid. Naturally
fragrance-free, the formula is friendly to sensitive skin.

15 ml e (0.5 fl. oz.)